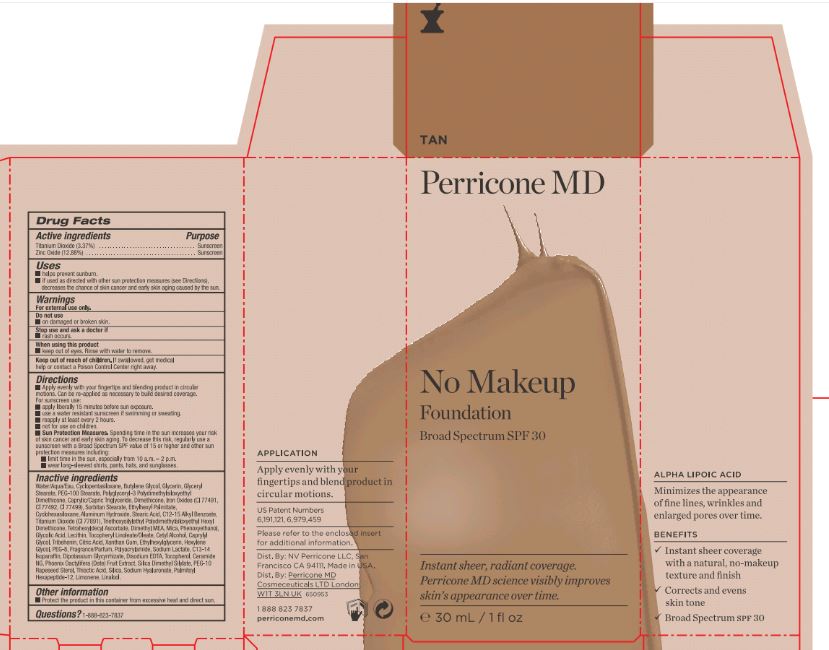 DRUG LABEL: No Makeup Foundation Tan Broad Spectrum SPF 30
NDC: 62742-4104 | Form: CREAM
Manufacturer: Allure Labs, Inc
Category: otc | Type: HUMAN OTC DRUG LABEL
Date: 20171201

ACTIVE INGREDIENTS: ZINC OXIDE 128.8 mg/1 mL; TITANIUM DIOXIDE 33.7 mg/1 mL
INACTIVE INGREDIENTS: WATER; CYCLOMETHICONE 5; BUTYLENE GLYCOL; GLYCERIN; GLYCERYL MONOSTEARATE; PEG-100 STEARATE; POLYGLYCERYL-3 POLYDIMETHYLSILOXYETHYL DIMETHICONE (4000 MPA.S); MEDIUM-CHAIN TRIGLYCERIDES; DIMETHICONE; SORBITAN MONOSTEARATE; ETHYLHEXYL PALMITATE; CYCLOMETHICONE 6; ALUMINUM HYDROXIDE; STEARIC ACID; ALKYL (C12-15) BENZOATE; TETRAHEXYLDECYL ASCORBATE; DEANOL; MICA; PHENOXYETHANOL; GLYCOLIC ACID; FERRIC OXIDE RED; FERRIC OXIDE YELLOW; FERROSOFERRIC OXIDE; LECITHIN, SOYBEAN; .ALPHA.-TOCOPHEROL LINOLEATE, D-; CETYL ALCOHOL; CAPRYLYL GLYCOL; TRIBEHENIN; CITRIC ACID MONOHYDRATE; XANTHAN GUM; ETHYLHEXYLGLYCERIN; HEXYLENE GLYCOL; POLYETHYLENE GLYCOL 400; POLYACRYLAMIDE (1500 MW); SODIUM LACTATE; C13-14 ISOPARAFFIN; GLYCYRRHIZINATE DIPOTASSIUM; EDETATE DISODIUM; TOCOPHEROL; CERAMIDE NG; DATE; SILICA DIMETHYL SILYLATE; PEG-10 RAPESEED STEROL; THIOCTIC ACID; SILICON DIOXIDE; HYALURONATE SODIUM; PALMITOYL HEXAPEPTIDE-12; LIMONENE, (+)-; LINALOOL, (+)-

DRUG FACTS

Active Ingredients:

Zinc Oxide: 12.88 %

Titanium Dioxide: 3.37%

PURPOSE

Sunscreen

Uses:

- help prevent sunburn.
- if used as directed with other sun protection measures (see directions), decreases the chance of skin cancer and early skin aging caused by the sun.

WARNINGS

For external use only.

DO NOT USE

on damaged or broken skin.

Do not use and ask a doctor if

- rash occurs

WHEN USING

- keep out of eyes. Rinse with water to remove.

KEEP OUT OF REACH OF CHILDREN

If swallowed, get a midical help or contact a Poison Control Center right away.

DOSAGE AND ADMINISTRATION

DirectionsApply evenly with your fingertips and blending product in circular motions. Can be re-applied as necessary to build desired coverage.

For sunscreen use:apply liberally 15 minutes before sun exposure.use water resistant sunscreen if swimming or sweating.reapply at least every 2 hours.not for use on children.Sun Protection Measures. Spending time in the sun increase your risk to skin cancer and early skin aging. To decrease this risk, regularly use a sunscreen with a Broad Spectrum SPF value of 15 or higher and other sun protection measures including: limit time in the sun, especially from 10 a.m. - 2 p.m.wear long-sleeved shirts, pants, hats, and sunglasses.

Inactive Ingredients:

Water/Aqua/Eau, cyclopentasiloxane, Butylene Glycol, Glycerin, Glyceryl Stearate, PEG-100 Stearate, Polyglyceryl-3 Polydimethylsiloxyethyl Dimethicone, caprylic/Capric Triglyceride, Dimethicone, Sorbitan Stearate, Ethylhexyl palmitate, Cyclohexasiloxane, Aluminum Hydroxide, Stearic Acid, C12-15 Alkyl Benzoate, Triethoxysilylethyl Polydimethyliloxyethyl Hexyl Dimethicone, Tetrhexyldecyl Ascorbate, Dimethyl MEA, Mica, Phenoxyethanol, Glycolic Acid, Iron Oxides (CI 77491, CI 77492, CI 77499), Lecithin, Tocopheryl Linoleate/Oleate, Cetyl Alcohol, Caprylyl Glycol, Tribeheniin, citric Acid, Xanthan Gum, Ethylhexylglycerin, Hexylene Glycol, PEG-8, Fragrance/Parfum, Polyacrylamide, Sodium Lactate, C13-14 Isoparaffin, Dipotassium Glycyrrhizate, Disodium ESTA, Tocopherol, Ceramide NG, Phoenix Dactylifera (Date) Fruit Extract, Silica Dimethyl Silylate, PEG-10 rapeseed Sterol, Thioctic acid, Silica, Sodiu Hylarunate, Palmitoyl Hexapeptide-12, Limonene, Linalool

OTHER SAFETY INFORMATION

Protect the product in this container from excessive heat and direct sun.

PACKAGE LABEL

Dist By:NV Perricone LLC

San Francisco, CA 94111

Made in USA

18888237837

perriconemd.com